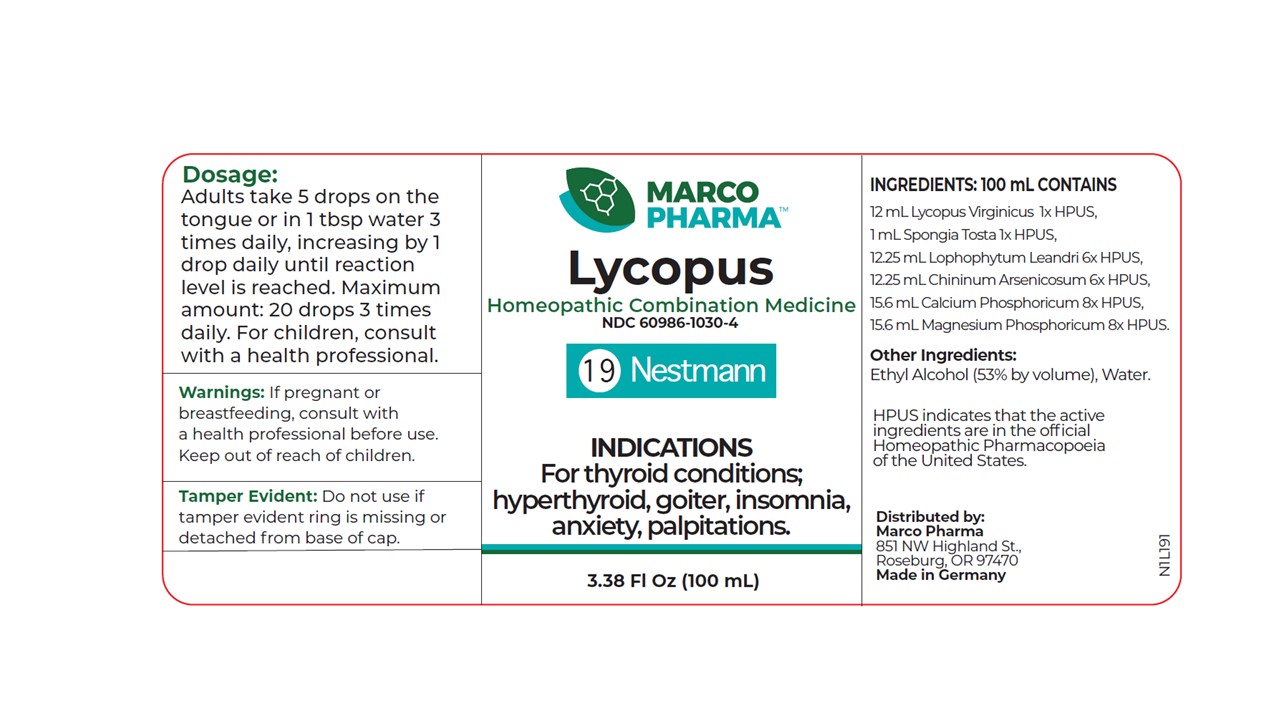 DRUG LABEL: LYCOPUS
NDC: 60986-1030 | Form: LIQUID
Manufacturer: Marco Pharma International LLC.
Category: homeopathic | Type: HUMAN OTC DRUG LABEL
Date: 20260112

ACTIVE INGREDIENTS: LYCOPUS VIRGINICUS 1 [hp_X]/100 mL; SPONGIA OFFICINALIS SKELETON, ROASTED 1 [hp_X]/100 mL; LOPHOPHYTUM LEANDRII 6 [hp_X]/100 mL; QUININE ARSENITE 6 [hp_X]/100 mL; TRIBASIC CALCIUM PHOSPHATE 8 [hp_X]/100 mL; MAGNESIUM PHOSPHATE, DIBASIC TRIHYDRATE 8 [hp_X]/100 mL
INACTIVE INGREDIENTS: ALCOHOL; WATER

Drug Facts

Active Ingredients

Bugleweed 1X HPUS

Sponge 1X HPUS

Stone Blossom 6X HPUS

Quinine 6X HPUS

Tribasic calcium phosphate 8X HPUS

Magnesium hydrogen phosphate 8X HPUS

The letters HPUS indicates that the components in this product are officially monographed in the Homeopathic Pharmacopoeia of United Sates.

Purpose

For thyroid conditions: hyperthyroid with palpitations.

Keep out of reach of children.

Dosage

Adults take 5 drops on the tongue or in 1 tablespoon water 3 times daily, increasing by one drop daily until reaction level is reached. Maxixum amount: 20 drops three times daily. Children receive 1/2 or less of the adult amount.

Warnings

If pregnant or breast-feeding, consult a health professional before use.

DOSAGE AND ADMINISTRATION

(Read Suggested Use Section)

Inactive Ingredients

Ethyl Alcohol (53% by vol.) and Water